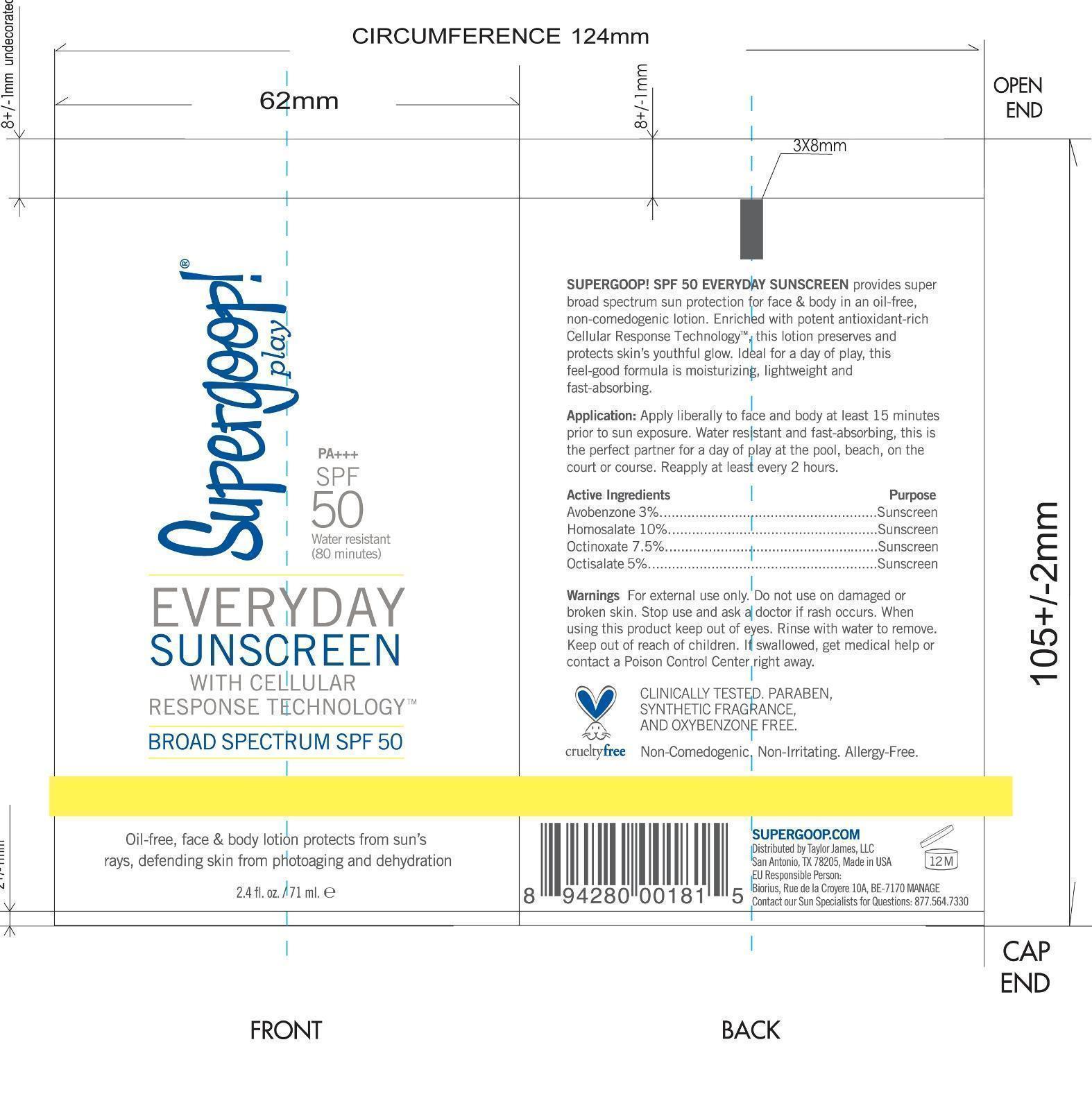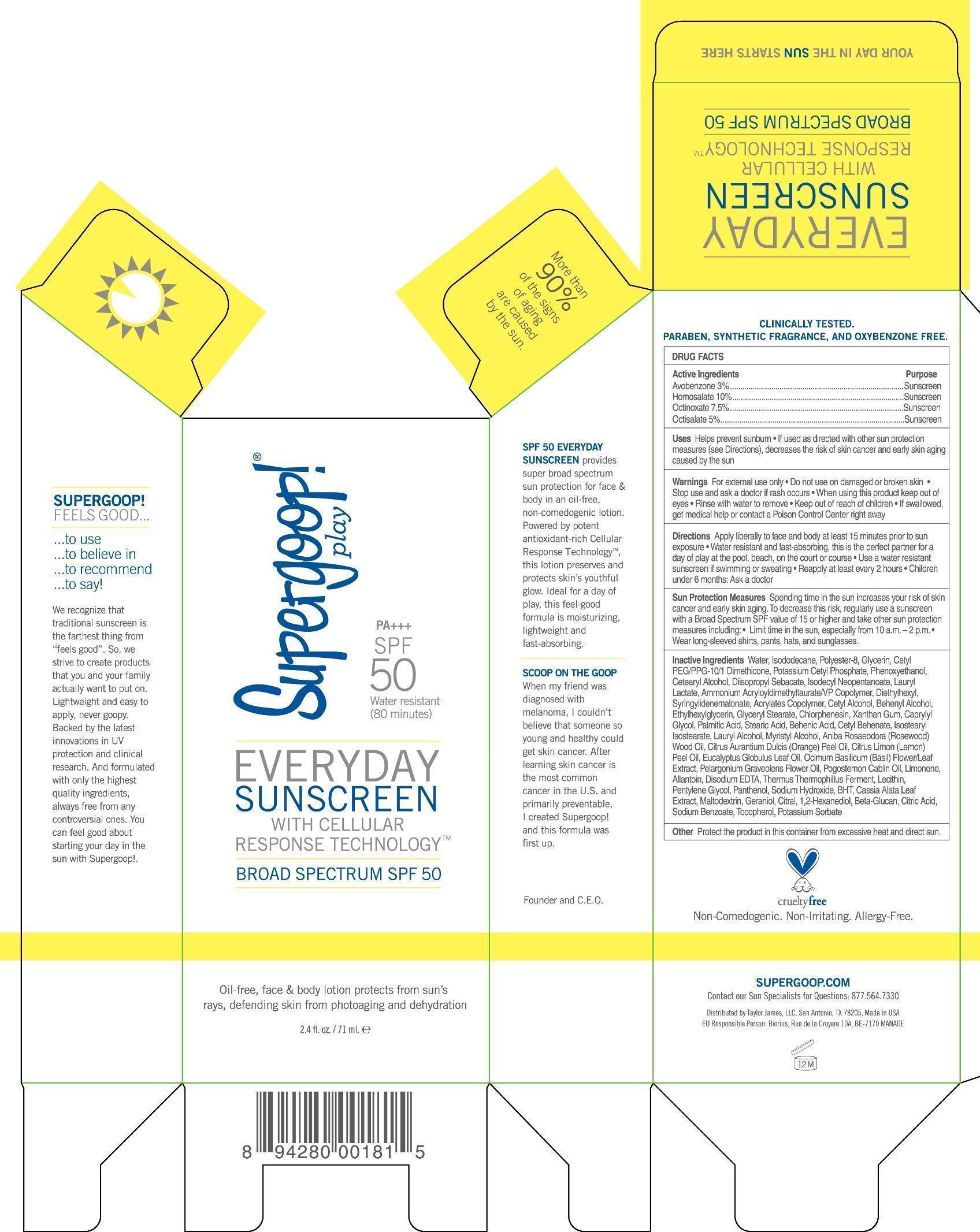 DRUG LABEL: Everyday Sunscreen SPF 50
NDC: 75936-135 | Form: LOTION
Manufacturer: TAYLOR JAMES, LTD.
Category: otc | Type: HUMAN OTC DRUG LABEL
Date: 20170105

ACTIVE INGREDIENTS: AVOBENZONE 3 g/100 mL; HOMOSALATE 10 g/100 mL; OCTINOXATE 7.5 g/100 mL; OCTISALATE 5 g/100 mL
INACTIVE INGREDIENTS: WATER; ISODODECANE; POLYESTER-8 (1400 MW, CYANODIPHENYLPROPENOYL CAPPED); GLYCERIN; CETYL PEG/PPG-10/1 DIMETHICONE (HLB 2); DIMETHICONE; POTASSIUM CETYL PHOSPHATE; PHENOXYETHANOL; CETOSTEARYL ALCOHOL; DIISOPROPYL SEBACATE; ISODECYL NEOPENTANOATE; LAURYL LACTATE; AMMONIUM ACRYLOYLDIMETHYLTAURATE/VP COPOLYMER; DIETHYLHEXYL SYRINGYLIDENEMALONATE; CETYL ALCOHOL; DOCOSANOL; ETHYLHEXYLGLYCERIN; GLYCERYL MONOSTEARATE; CHLORPHENESIN; XANTHAN GUM; CAPRYLYL GLYCOL; PALMITIC ACID; STEARIC ACID; BEHENIC ACID; CETYL BEHENATE; ISOSTEARYL ISOSTEARATE; LAURYL ALCOHOL; MYRISTYL ALCOHOL; ROSEWOOD OIL; ORANGE OIL; EUCALYPTUS OIL; OCIMUM BASILICUM FLOWERING TOP; PELARGONIUM GRAVEOLENS FLOWER OIL; POGOSTEMON CABLIN TOP; LIMONENE, (+)-; ALLANTOIN; EDETATE SODIUM; THERMUS THERMOPHILUS LYSATE; LECITHIN, SOYBEAN; PENTYLENE GLYCOL; PANTHENOL; SODIUM HYDROXIDE; BUTYLATED HYDROXYTOLUENE; SENNA ALATA LEAF; MALTODEXTRIN; GERANIOL; CITRAL; 1,2-HEXANEDIOL; CITRIC ACID MONOHYDRATE; SODIUM BENZOATE; TOCOPHEROL; POTASSIUM SORBATE

Everyday Broad Spectrum SPF 50

Active Ingredients Purpose

Avobenzone 3% Sunscreen

Homosalate 10% Sunscreen

Octinoxate 7.5% Sunscreen

Octisalate 5% Sunscreen

PURPOSE

Uses Helps Prevent Sunburn

If used as directed with other sun protection measures (see Directions), decreases the risk of Skin cancer and early skin aging caused by the sun

Keep out of reach of children.

Stop use and ask a doctor if rash occurs

WARNINGS

For External use only

Do not use on damaged or broken skin

When using this product, Keep out of eyes. Rinse with water to remove

If swallowed, get medical help or contact a Poison Control Center right away

Directions

Apply Liberally to face and and body at least 15 minutes prior to sun exposure. water resistant

INACTIVE INGREDIENT

Inactive Ingredients Water, Isododecane, Polyester-8, Glycerin, Cetyl PEG/PPG-10/1 Dimethicone, Potassium Cetyl Phosphate, Phenoxyethanol, Cetearyl alcohol, Diisopropyl Sebacate, Isodecyl Neopentanoate, Lauryl Lactate, Ammonium Acryloyldimethyltaurate/VP Copolymer, Diethylhexyl, Syringylidenemalonate, Acrylates Copolymer, Cetyl Alcohol, Beheneyl Alcohol, Ethylhexylglycerin, Glyceryl Stearate, Chlorpehensin, Xanthan Gum, Caprylyl Glycol, Palmitic Acid, Stearic Acid, Behenic Acid, Cetyl Behenate, Isostearyl Isostearate, Lauryl Alcohol, Myristyl Alcohol, Aniba Rosaeodora (Rosewood) Wood Oil, Citrus Aurantium Dulcis (Orange) Peel Oil, Citrus Limon (Lemon) Peel Oil, Eucalyptus Globulus Leaf Oil, Ocimum Bascilicum (Basil) Flower/Leaf Extract, Pelargonium Graveolens Flower Oil, Pogostemon Cablin Oil, Limonene, Allantoin, Disodium EDTA, Thermus Thermophillus Ferment, Lecithin, Pentylene Glycol, Panthenol, Sodium Hydroxide, BHT, Cassia Alata Leaf Extract, Maltodextrin, Gernaniol, Citral, 1,2-Hexandiol, Beta Glucan, Citric Acid, Sodium Benzoate, Tocopheryl, Potassium Sorbate

PACKAGE LABEL

Supergoop Play

SPF 50

Water Resistant (80 minutes)

Everyday Sunscreen with cellular response technology

Broad Spectrum SPF 50

Oil-free, face & body lotion protects from sun's rays, defending skin from photoaging

and dehydration

2.4 Fl. Oz. / 71 ml